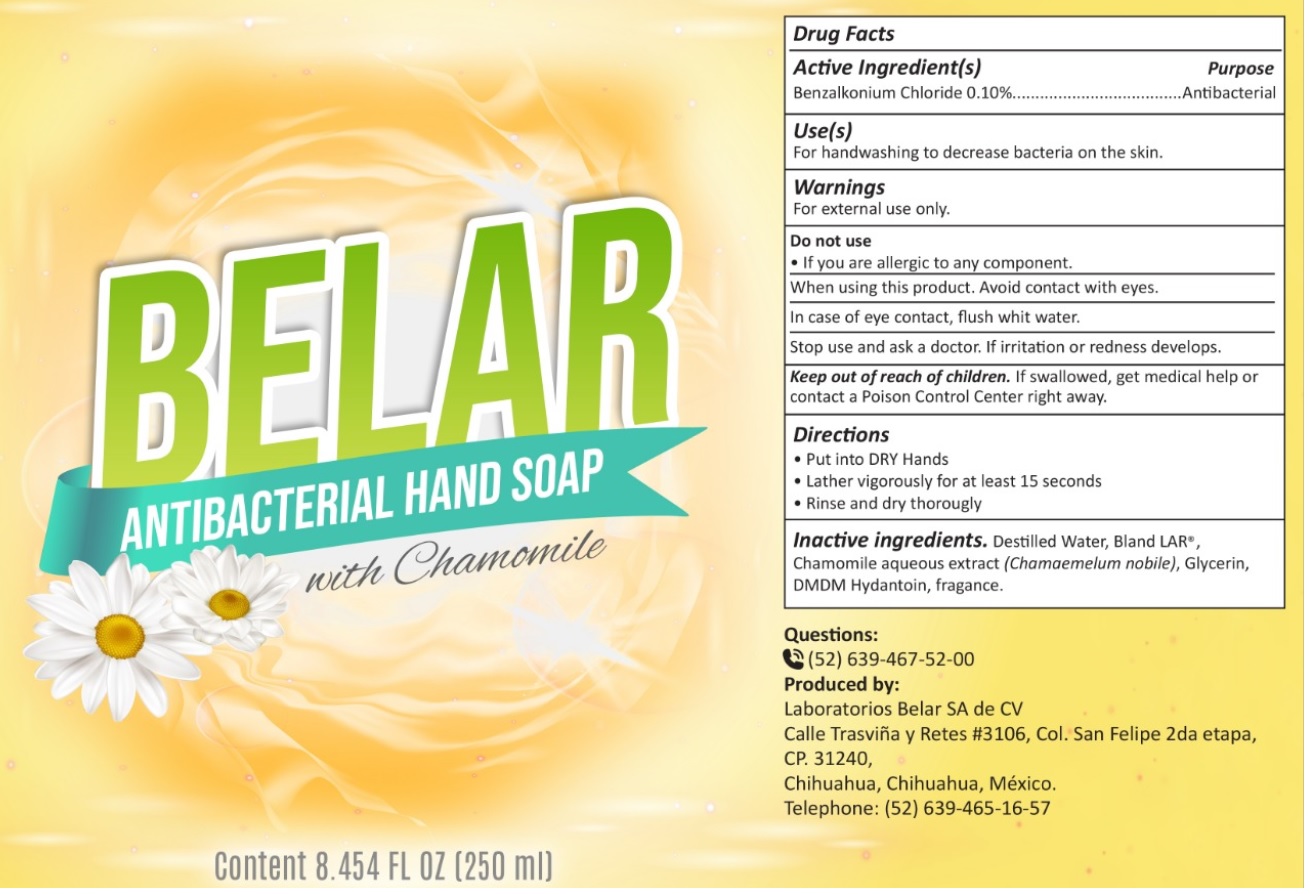 DRUG LABEL: Belar Antibacterial whith chamomile
NDC: 79716-000 | Form: LIQUID
Manufacturer: LABORATORIOS BELAR S.A. DE C.V.
Category: otc | Type: HUMAN OTC DRUG LABEL
Date: 20220106

ACTIVE INGREDIENTS: BENZALKONIUM CHLORIDE 1 mg/1 mL
INACTIVE INGREDIENTS: WATER; CHAMAEMELUM NOBILE WHOLE; GLYCERIN; DMDM HYDANTOIN

Belar Antibacterial soap whith chamomile

Active Ingredient(s)

Benzalkonium Chloride 0.10%

Purpose

Antibacterial

Use(s)

For handwashing to decrease bacteria on the skin.

Warnings

For external use only.

Do not use

- If you are allergic to any component.

When using this product.

Avoid contact with eyes. In case of eye contact, flush with water.

Stop use and ask a doctor.

If irritation or redness develops.

Keep out of reach of children.

If swallowed, get medical help or contact a Poison Control Center right away.

Directions

- Put into DRY Hands
- Lather vigorously for least 15 seconds
- Rinse and dry thoroughly

Inactive ingredients.

Destilled Water, Bland LAR®, Chamomile aqueous extract (Chamaemelum nobil), Glycerin, DMDM Hydantoin, fragance.